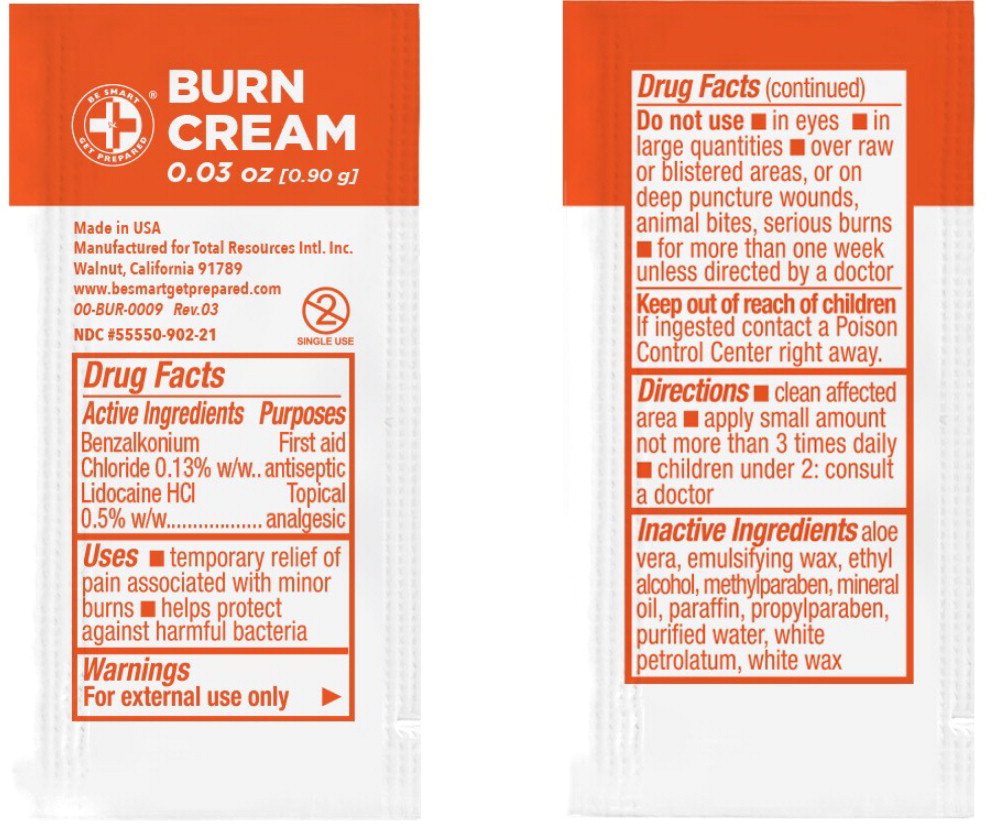 DRUG LABEL: Burn Cream
NDC: 55550-902 | Form: CREAM
Manufacturer: Total Resources International
Category: otc | Type: HUMAN OTC DRUG LABEL
Date: 20250418

ACTIVE INGREDIENTS: benzalkonium chloride
 1.3 mg/1 g; lidocaine hydrochloride
 5 mg/1 g
INACTIVE INGREDIENTS: aloe vera leaf; alcohol; methylparaben; mineral oil; paraffin; propylparaben; water; petrolatum; white wax

Drug Facts

Active Ingredients

Benzalkonium Chloride 0.13% w/w

Lidocaine HCI 0.5% w/w

Purposes

First aid antiseptic

Topical analgesic

Uses

- temporary relief of pain associated with minor burns
- helps protect against harmful bacteria

Warnings

For external use only

Do not use

- in eyes
- in large quantities
- over raw or blistered areas, or on deep puncture wounds, animal bites, serious burns
- for more than one week unless directed by a doctor

Keep out of reach of children

If ingested contact a Poison Control Center right away.

Directions

- clean affected area
- apply small amount not more than 3 times daily
- children under 2: consult a doctor

Inactive Ingredients

aloe vera, emulsifying wax, ethyl alcohol, methylparaben, mineral oil, paraffin, propylparaben, purified water, white petrolatum, white wax

Principal Display Panel – 0.03 oz Pouch Label

BE SMART

GET PREPARED®

BURN CREAM

0.03 oz [0.90 g]

Single Use

Made in USA

Manufactured for Total Resources Intl. Inc.

Walnut, California 91789

www.besmartgetprepared.com • 00-BUR-0009 Rev. 03

NDC 55550-902-21